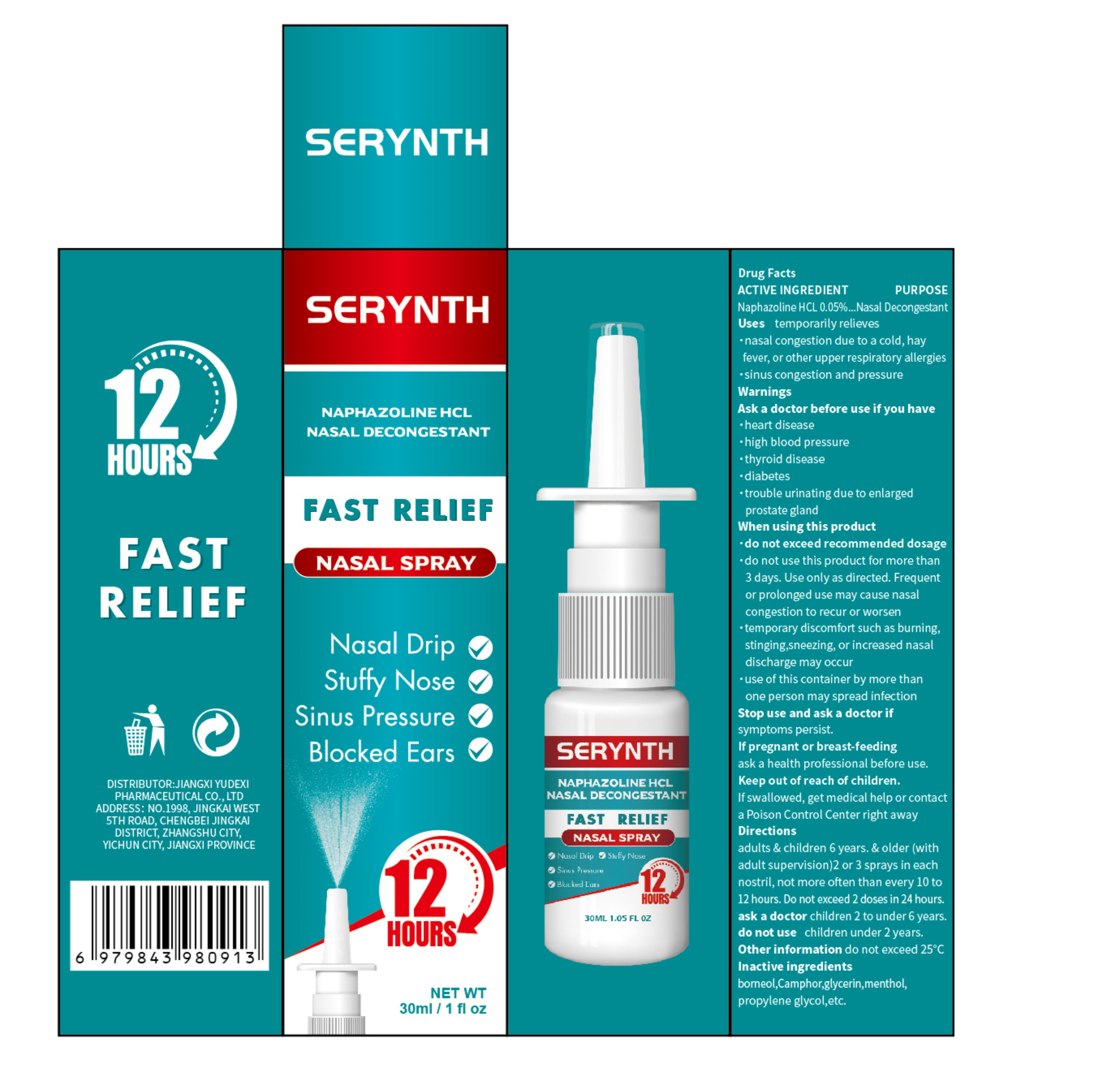 DRUG LABEL: SERYNTH FAST RELIEF NASAL
NDC: 85248-099 | Form: SPRAY
Manufacturer: Jiangxi Yudexi Pharmaceutical Co., LTD
Category: otc | Type: HUMAN OTC DRUG LABEL
Date: 20260208

ACTIVE INGREDIENTS: NAPHAZOLINE HCL 0.05 g/100 mL
INACTIVE INGREDIENTS: MENTHOL; BORNEOL; PROPYLENE GLYCOL; CAMPHOR (SYNTHETIC); GLYCERIN

85248-099

Active Ingredient

Naphazoline HCL 0.05%.

Purpose

Nasal Decongestant

Use

temporarily relieves ·nasal congestion due to a cold, hay fever, or other upper respiratory allergies ·sinus congestion and pressure

Warnings

Ask a doctor before use if you have ·heart disease ·high blood pressure
.thyroid disease
·diabetes
·trouble urinating due to enlarged prostate gland

Do not use

·do not exceed recommended dosage ·do not use this product for more than 3 days. Use only as directed. Frequent or prolonged use may cause nasal congestion to recur or worsen ·temporary discomfort such as burning, stinging,sneezing, or increased nasaldischarge may occur
·use of this container by more than one person may spread infection chidren under 2 years.

When Using

·do not exceed recommended dosage ·do not use this product for more than 3 days. Use only as directed. Frequent or prolonged use may cause nasal congestion to recur or worsen ·temporary discomfort such as burning, stinging,sneezing, or increased nasaldischarge may occur
·use of this container by more than one person may spread infection

Stop Use

Stop use and ask a doctor if symptoms persist.

Ask Doctor

If pregnant or breast-feeding, ask a health professional before use. children 2 to under 6 years.

Keep Oot Of Reach Of Children

If swallowed,get medical help or contact a Poison Control Center right away

Directions

adults&children 6 years &older(with adult supervision): 2 or 3 sprays in each nostril, not more often than every 10 to 12 hours.Do not exceed 2 doses in 24 hours

Other information

do not exceed 25°C.

Inactive ingredients

borneol,Camphor,glycerin,menthol，propylene glycol,etc.